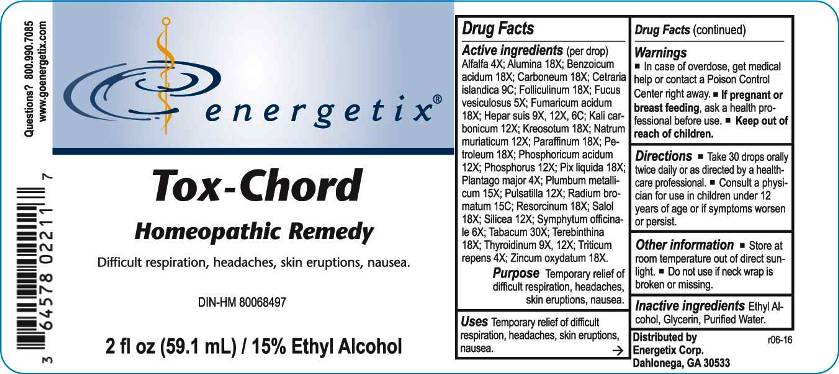 DRUG LABEL: Tox-Chord
NDC: 64578-0132 | Form: LIQUID
Manufacturer: Energetix Corp
Category: homeopathic | Type: HUMAN OTC DRUG LABEL
Date: 20161111

ACTIVE INGREDIENTS: ALFALFA 4 [hp_X]/1 mL; ALUMINUM OXIDE 18 [hp_X]/1 mL; BENZOIC ACID 18 [hp_X]/1 mL; D&C BLACK NO. 2 18 [hp_X]/1 mL; CETRARIA ISLANDICA SUBSP. ISLANDICA 9 [hp_C]/1 mL; ESTRONE 18 [hp_X]/1 mL; FUCUS VESICULOSUS 5 [hp_X]/1 mL; FUMARIC ACID 18 [hp_X]/1 mL; PORK LIVER 9 [hp_X]/1 mL; POTASSIUM CARBONATE 12 [hp_X]/1 mL; WOOD CREOSOTE 18 [hp_X]/1 mL; SODIUM CHLORIDE 12 [hp_X]/1 mL; PARAFFIN 18 [hp_X]/1 mL; KEROSENE 18 [hp_X]/1 mL; PHOSPHORIC ACID 12 [hp_X]/1 mL; PHOSPHORUS 12 [hp_X]/1 mL; PINE TAR 18 [hp_X]/1 mL; PLANTAGO MAJOR 4 [hp_X]/1 mL; LEAD 15 [hp_X]/1 mL; PULSATILLA VULGARIS 12 [hp_X]/1 mL; RADIUM BROMIDE 15 [hp_C]/1 mL; RESORCINOL 18 [hp_X]/1 mL; PHENYL SALICYLATE 18 [hp_X]/1 mL; SILICON DIOXIDE 12 [hp_X]/1 mL; COMFREY ROOT 6 [hp_X]/1 mL; TOBACCO LEAF 30 [hp_X]/1 mL; TURPENTINE OIL 18 [hp_X]/1 mL; THYROID, BOVINE 9 [hp_X]/1 mL; ELYMUS REPENS ROOT 4 [hp_X]/1 mL; ZINC OXIDE 18 [hp_X]/1 mL
INACTIVE INGREDIENTS: WATER; ALCOHOL

Drug Facts:

Active ingredients (per drop):

Alfalfa 4X; Alumina 18X; Benzoicum Acidum 18X; Carboneum 18; Cetraria Islandica 9C; Folliculinum 18X; Fucus Vesiculosus 5X; Fumaricum Acidum 18X; Hepar Suis 9X, 12X, 6C; Kali Carbonicum 12X; Kreosotum 18X; Natrum Muriaticum 12X; Paraffinum 18X; Petroleum 18X; Phosphoricum Acidum 12X; Phosphorus 12X; Pix Liquida 18X; Plantago Major 4X; Plumbum Metallicum 15X; Pulsatilla (Vulgaris) 12X; Radium Bromatum 15C; Resorcinum 18X; Salol 18X; Silicea 12X; Symphytum Officinale 6X; Tabacum 30X; Terebinthina 18X; Thyroidinum (Bovine) 9X, 12X; Triticum Repens 4X; Zincum Oxydatum 18X.

Purpose:

Temporary relief of difficult respiration, headaches, skin eruptions, nausea.

Warnings:

In case of overdose, get medical help or contact a Poison Control Center right away.
If pregnant or breast feeding, ask a health professional before use.
Keep out of reach of children.

Other information
Store in a cool, dry place out of direct sunlight.
Do not use if neck wrap is broken or missing.

Keep out of reach of children. In case of overdose, get medical help or contact a Poison Control Center right away.

Directions:

Take 30 drops orally twice daily or as directed by a healthcare professional.
Consult a physician for use in children under 12 years of age or if symptoms worsen or persist.

Uses:

Temporary relief of difficult respiration, headaches, skin eruptions, nausea.

Inactive ingredients:

Ethyl Alcohol, Glycerin, Purified Water.

Questions:

Distributed by
Energetix Corp.
Dahlonega, GA 30533

Questions? 800.990.7085
www.goenergetix.com

Package Label Display:

energetix

Tox-Chord

Homeopathic Remedy

Difficult respiration, headaches, skin eruptions, nausea.

2 fl oz (59.1 mL)